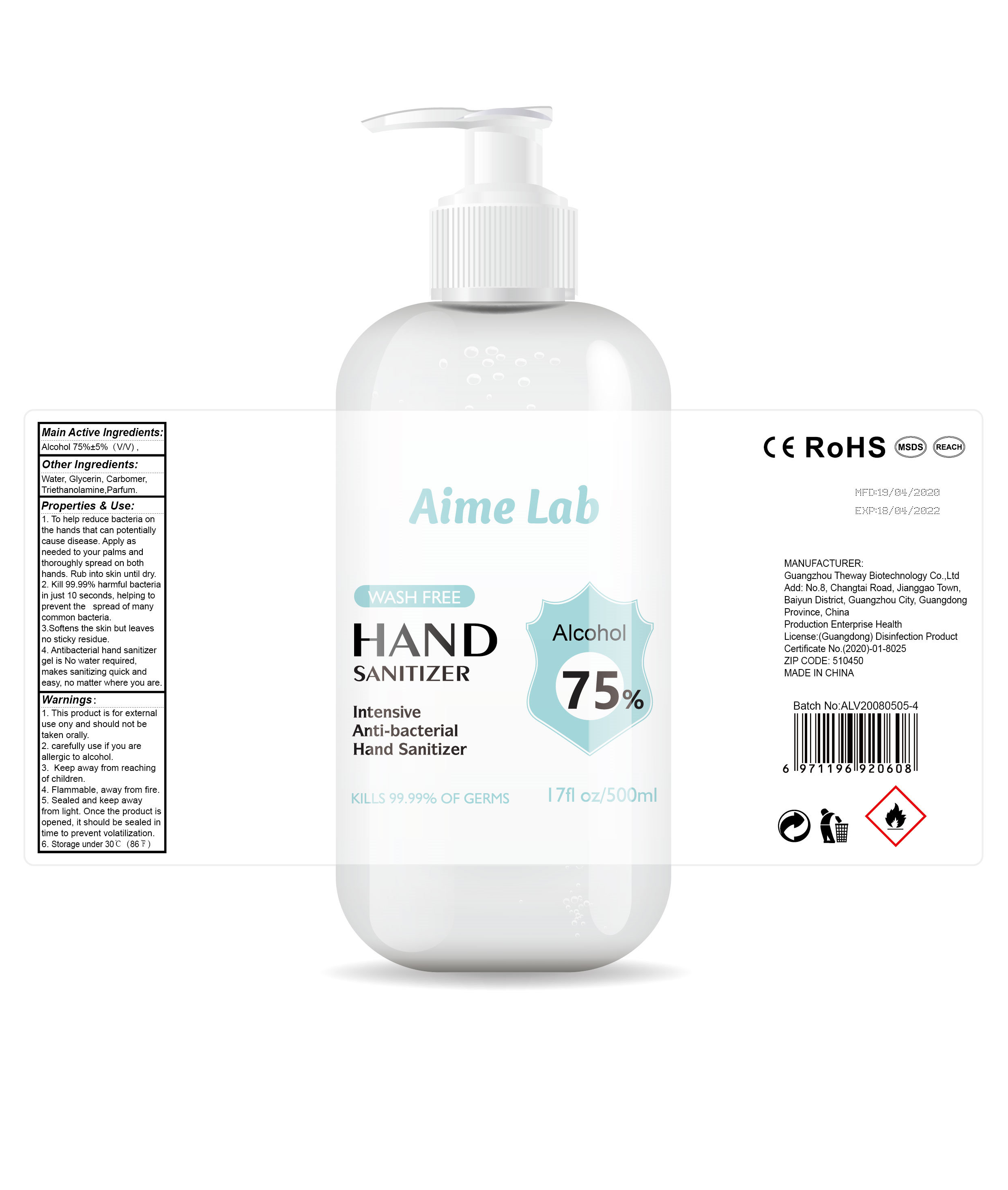 DRUG LABEL: Hand Sanitizer
NDC: 41875-002 | Form: GEL
Manufacturer: Guangzhou Theway Biotechnology Co., Ltd.
Category: otc | Type: HUMAN OTC DRUG LABEL
Date: 20200806

ACTIVE INGREDIENTS: ALCOHOL 375 mL/500 mL
INACTIVE INGREDIENTS: WATER; CARBOMER HOMOPOLYMER, UNSPECIFIED TYPE; FRAGRANCE LAVENDER & CHIA F-153480; TROLAMINE; GLYCERIN

DOSAGE AND ADMINISTRATION

Storage under 30°C (86°F).

INACTIVE INGREDIENT

Water,Glycerin,Carbomer,Triethanolamine,Parfum

INDICATIONS AND USAGE

Thoroughly wipe hands, fingers and wrists.

ACTIVE INGREDIENT

Alcohol

keep out of reach of children

PURPOSE

Disinfection
Sterilization
No Rinseing

WARNINGS

1. This product is for external use ony and should not be taken orally.
2. carefully use if you are allergic to alcohol.
3. Keep away from reaching of children.
4. Flammable, away from fire.
5. Sealed and keep away from light. Once the product is opened, it should be soaled in time to prevent volatilization.
6. Storage under 30°C (86°F)